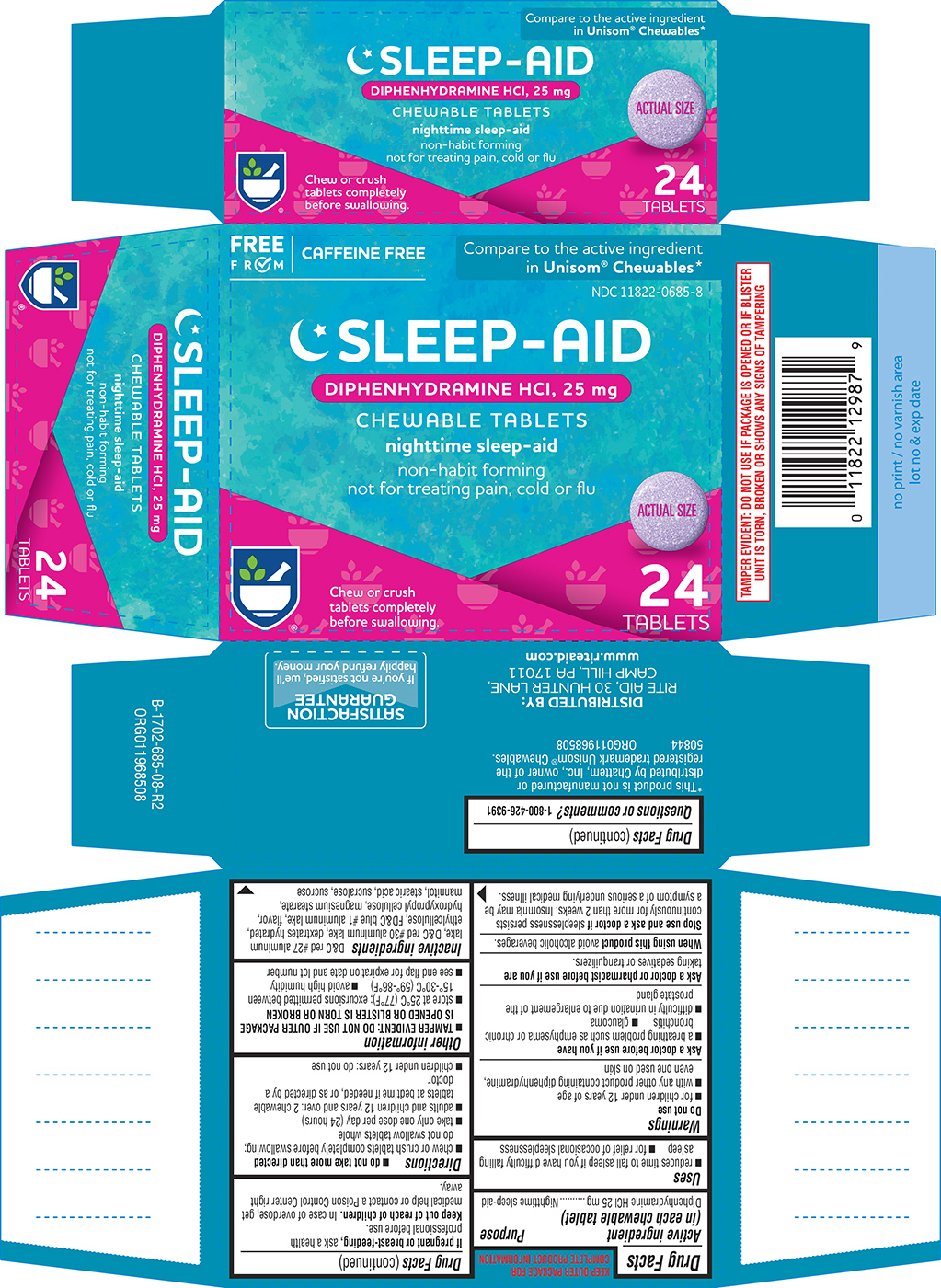 DRUG LABEL: Sleep-Aid
NDC: 11822-0685 | Form: TABLET, CHEWABLE
Manufacturer: Rite Aid Corporation
Category: otc | Type: HUMAN OTC DRUG LABEL
Date: 20250612

ACTIVE INGREDIENTS: DIPHENHYDRAMINE HYDROCHLORIDE 25 mg/1 1
INACTIVE INGREDIENTS: D&C RED NO. 27 ALUMINUM LAKE; D&C RED NO. 30; DEXTROSE MONOHYDRATE; ETHYLCELLULOSE, UNSPECIFIED; FD&C BLUE NO. 1 ALUMINUM LAKE; HYDROXYPROPYL CELLULOSE, UNSPECIFIED; MAGNESIUM STEARATE; MANNITOL; STEARIC ACID; SUCRALOSE; SUCROSE

Rite Aid 44-685

Active ingredient (in each chewable tablet)

Diphenhydramine HCl 25 mg

Purpose

Nighttime sleep-aid

Uses

- reduces time to fall asleep if you have difficulty falling asleep
- for relief of occasional sleeplessness

Warnings

Do not use

- for children under 12 years of age
- with any other product containing diphenhydramine, even one used on skin

Ask a doctor before use if you have

- a breathing problem such as emphysema or chronic bronchitis
- glaucoma
- difficulty in urination due to enlargement of the prostate gland

Ask a doctor or pharmacist before use if you are

taking sedatives or tranquilizers.

When using this product

avoid alcoholic beverages.

Stop use and ask a doctor if

sleeplessness persists continuously for more than 2 weeks. Insomnia may be a symptom of a serious underlying medical illness.

If pregnant or breast-feeding,

ask a health professional before use.

Keep out of reach of children.

In case of overdose, get medical help or contact a Poison Control Center right away.

Directions

- do not take more than directed
- chew or crush tablets completely before swallowing; do not swallow tablets whole
- take only one dose per day (24 hours)
- adults and children 12 years and over: 2 chewable tablets at bedtime if needed, or as directed by a doctor
- children under 12 years: do not use

Other information

- TAMPER EVIDENT: DO NOT USE IF OUTER PACKAGE IS OPENED OR BLISTER IS TORN OR BROKEN
- store at 25°C (77°F); excursions permitted between 15°-30°C (59°-86°F)
- avoid high humidity
- see end flap for expiration date and lot number

Inactive ingredients

D&C red #27 aluminum lake, D&C red #30 aluminum lake, dextrates hydrated, ethylcellulose, FD&C blue #1 aluminum lake, flavor, hydroxypropyl cellulose, magnesium stearate, mannitol, stearic acid, sucralose, sucrose

Questions or comments?

1-800-426-9391

Principal display panel

FREE
FROM
CAFFEINE FREE

Compare to the active ingredient
in Unisom® Chewables*

NDC 11822-0685-8

SLEEP-AID
DIPHENHYDRAMINE HCI, 25 mg
CHEWABLE TABLETS
nighttime sleep-aid
non-habit forming
not for treating pain, cold or flu

ACTUAL SIZE

Chew or crush
tablets completely
before swallowing.

ACTUAL SIZE

24
TABLETS

TAMPER EVIDENT: DO NOT USE IF PACKAGE IS OPENED OR IF BLISTER
UNIT IS TORN, BROKEN OR SHOWS ANY SIGNS OF TAMPERING

*This product is not manufactured or
distributed by Chattem, Inc., owner of the
registered trademark Unisom® Chewables.
50844 ORG011968508

DISTRIBUTED BY:
RITE AID, 30 HUNTER LANE,
CAMP HILL, PA 17011
www.riteaid.com

SATISFACTION
GUARANTEE
If you’re not satisfied, we’ll
happily refund your money.

Rite Aid 44-685